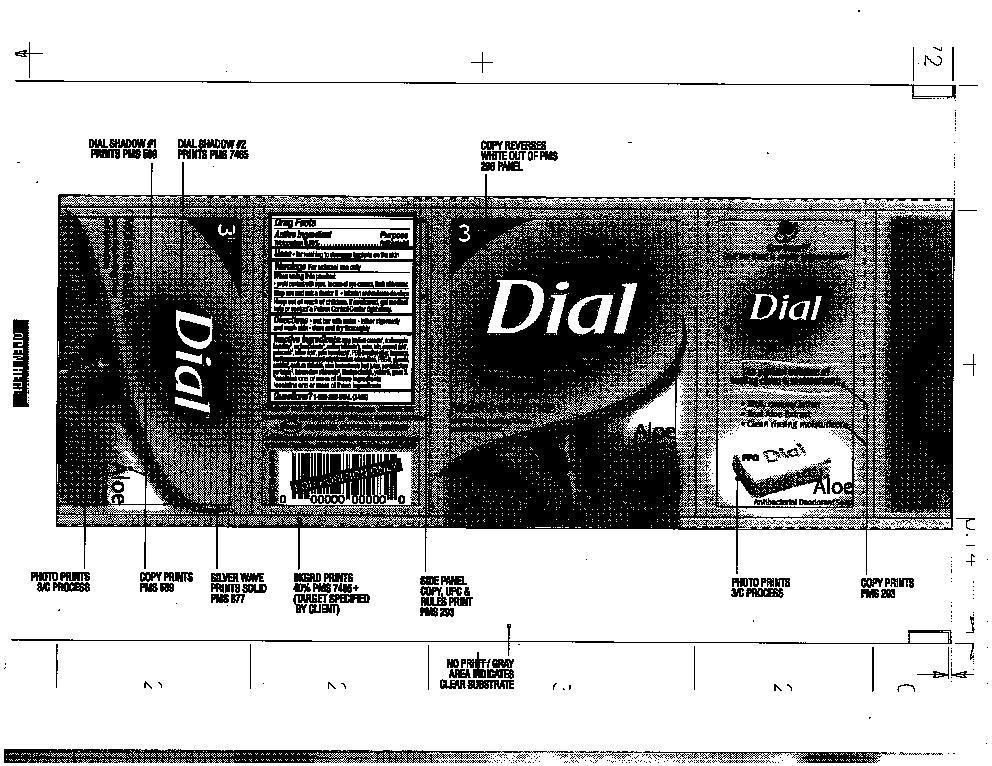 DRUG LABEL: Dial Aloe 
NDC: 51815-302 | Form: SOAP
Manufacturer: VVF Illinois Services LLC
Category: otc | Type: HUMAN OTC DRUG LABEL
Date: 20140527

ACTIVE INGREDIENTS: TRICLOCARBAN 1.017 g/339 g
INACTIVE INGREDIENTS: SODIUM COCOATE; SODIUM PALM KERNELATE; SODIUM PALMATE; SODIUM TALLOWATE, BEEF; WATER; TALC; COCONUT ACID; PALM ACID; TALLOW ACID, BEEF; PALM KERNEL ACID; PEG-6 METHYL ETHER; SUNFLOWER SEED OIL GLYCERETH-8 ESTERS; PEG-9 DIMETHICONE (400 CST); GLYCERIN; SORBITOL; SODIUM CHLORIDE; ALOE VERA LEAF; PENTASODIUM PENTETATE; ETIDRONATE TETRASODIUM; TITANIUM DIOXIDE; FD&C YELLOW NO. 5; FD&C GREEN NO. 3

Dial Aloe

Active ingredient

Triclocarban 0.30%

PURPOSE

ANTIBACTERIAL

KEEP OUT OF REACH OF CHILDREN

If swallowed, get medical

help or contact Poison Control right away.

USE

For washing to decrease bacteria on the skin

WARNINGS

For external use only

When using this product

Avoid contact with eyes. In case of eye contact, flush with water

Stop using and ask doctor if irritation and redness develops

DOSAGE AND ADMINISTRATION

wet bar with water - lather vigorously -

and wash skin - rinse and dry thoroughly

INACTIVE INGREDIENTS

SOAP, (SODIUM COCOATE*, SODIUM PALM KERNELATE*, SODIUM PALMATE*, SODIUM TALLOWATE*), WATER, TALC, COCONUT ACID*, PALM ACID*, TALLOW ACID, PALM KERNEL ACID*, PEG-G METHYL ETHER, FRAGRANCE, SUNFLOWERSEEDAMIDOPROPYL ETHYLDIMONIUM ETHOSULFATE, PEG-9, GLYCERIN, SORBITOL, SODIUM CHLORIDE, ALOE BARBADENSIS LEAF JUICE, PENTASODIUM PENTETATE, TETRASODIUM ETIDRONATE, TITANIUM DIOXIDE, YELLOW 5, GREEN 3.

QUESTIONS

1-800-258- DIAL (3425)